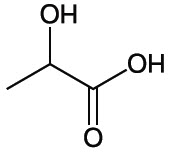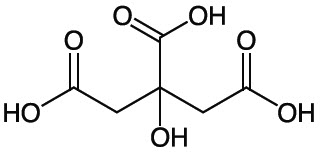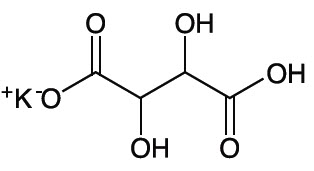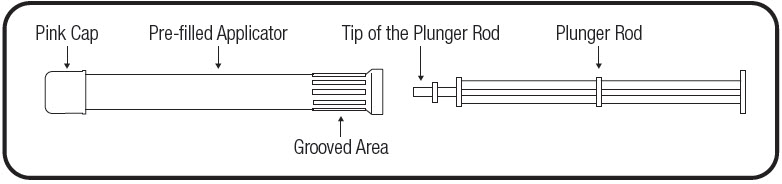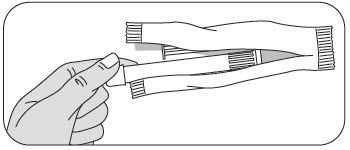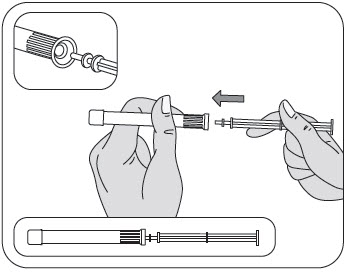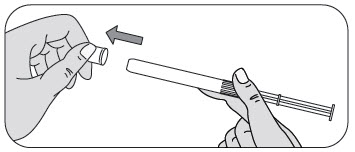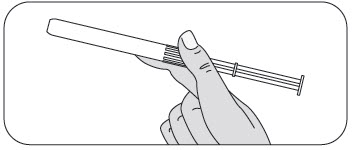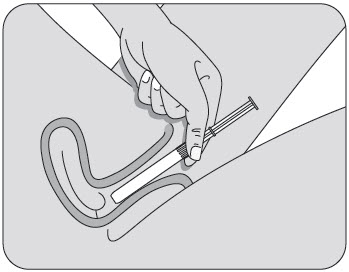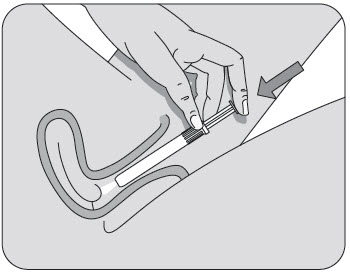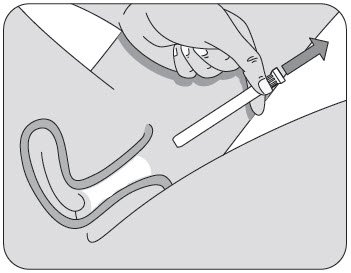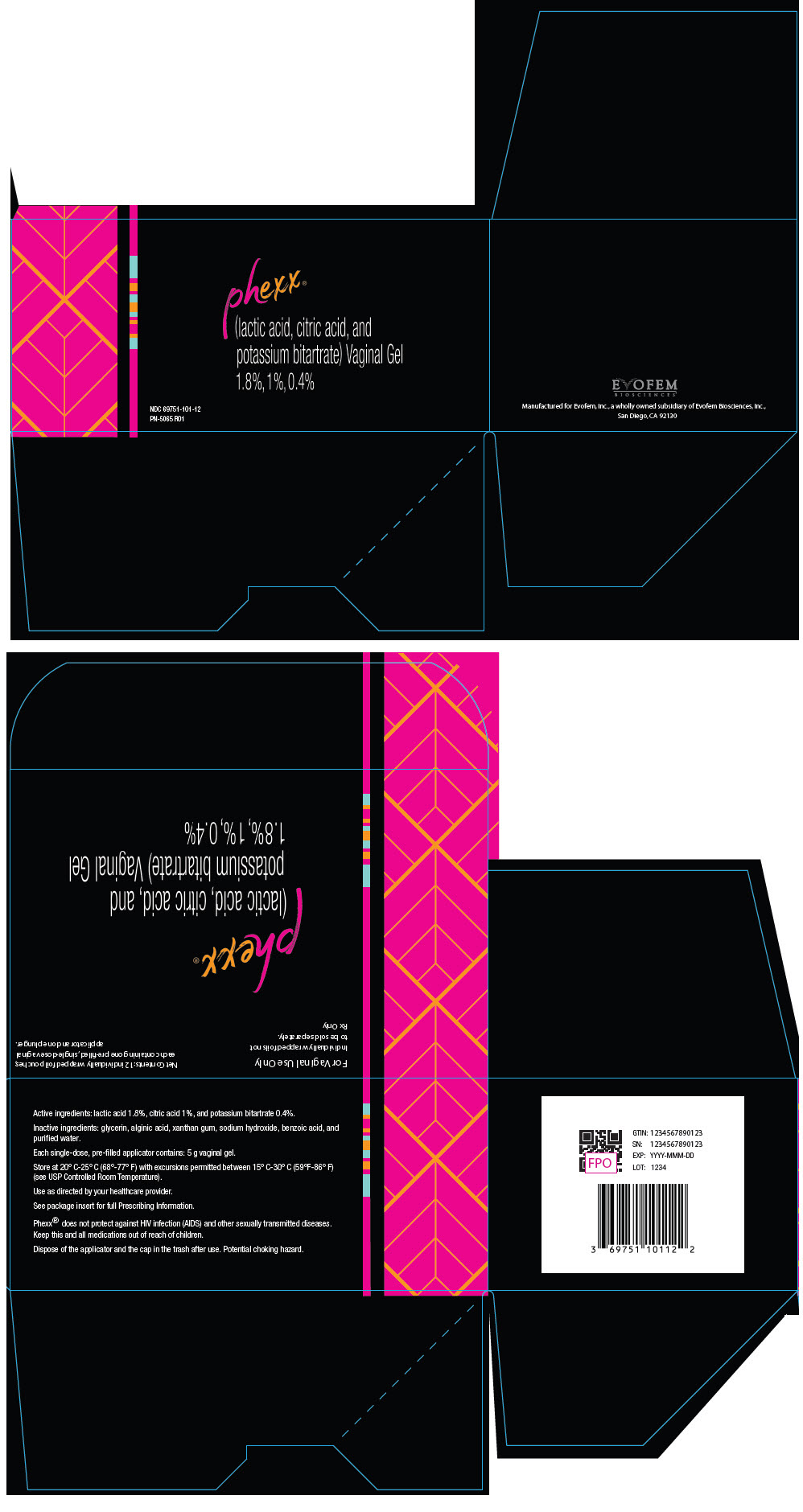 DRUG LABEL: Phexx
NDC: 69751-101 | Form: GEL
Manufacturer: Evofem, Inc.
Category: prescription | Type: HUMAN PRESCRIPTION DRUG LABEL
Date: 20250502

ACTIVE INGREDIENTS: LACTIC ACID, L- 90 mg/5 g; CITRIC ACID MONOHYDRATE 50 mg/5 g; POTASSIUM BITARTRATE 20 mg/5 g

HIGHLIGHTS OF PRESCRIBING INFORMATION

These highlights do not include all the information needed to use PHEXX® safely and effectively. See full prescribing information for PHEXX.
PHEXX (lactic acid, citric acid, and potassium bitartrate) vaginal gel
Initial U.S. Approval: 2020

1 INDICATIONS AND USAGE

PHEXX is a combination of lactic acid, citric acid, and potassium bitartrate indicated for the prevention of pregnancy in females of reproductive potential for use as an on-demand method of contraception. (1)

Limitations of Use: PHEXX is not effective for the prevention of pregnancy when administered after intercourse.

2 DOSAGE AND ADMINISTRATION

- Administer one (1) pre-filled single-dose applicator of PHEXX (5 grams) vaginally immediately before (or up to one hour before) each episode of vaginal intercourse (2.1)
- May use during any part of the menstrual cycle (2.2)

3 DOSAGE FORMS AND STRENGTHS

Each pre-filled single-dose vaginal applicator delivers 5 grams of gel containing lactic acid (1.8%), citric acid (1%), and potassium bitartrate (0.4%). (3)

5 WARNINGS AND PRECAUTIONS

- Cystitis and Pyelonephritis: Avoid use in women with a history of recurrent UTI or urinary tract abnormalities (5.1)

6 ADVERSE REACTIONS

Most common adverse reactions (≥2%) were vulvovaginal burning sensation, vulvovaginal pruritus, vulvovaginal mycotic infection, urinary tract infection, vulvovaginal discomfort, bacterial vaginosis, vaginal discharge, genital discomfort, dysuria, and vulvovaginal pain. (6.1)

To report SUSPECTED ADVERSE REACTIONS, contact Evofem at toll-free phone 1-833-EVFMBIO or FDA at 1-800-FDA-1088 or www.fda.gov/medwatch.

FULL PRESCRIBING INFORMATION

1 INDICATIONS AND USAGE

PHEXX is indicated for the prevention of pregnancy in females of reproductive potential for use as an on-demand method of contraception.

Limitations of Use

PHEXX is not effective for the prevention of pregnancy when administered after intercourse [see Dosage and Administration (2.1)].

2 DOSAGE AND ADMINISTRATION

2.1 Recommended Dosage

Administer one pre-filled applicator of PHEXX (5 grams) vaginally immediately before or up to one hour before each act of vaginal intercourse. If more than one act of vaginal intercourse occurs within one hour, an additional dose must be applied. Five grams of PHEXX contains 90 mg of lactic acid, 50 mg of citric acid, and 20 mg of potassium bitartrate.

2.2 Timing of PHEXX Use

May use PHEXX during any part of the menstrual cycle. May use PHEXX as soon as it is safe to resume vaginal intercourse after childbirth, abortion, or miscarriage.

2.3 Use of PHEXX with Other Contraceptive Methods

PHEXX may be used concomitantly with hormonal contraceptives; latex, polyurethane, and polyisoprene condoms; and vaginal diaphragms. Avoid PHEXX use with vaginal rings.

2.4 Use of PHEXX with Other Vaginal Products

PHEXX may be used concomitantly with other products for vaginal infections including miconazole, metronidazole, and tioconazole.

3 DOSAGE FORMS AND STRENGTHS

Vaginal gel: 18 mg of lactic acid, 10 mg of citric acid, and 4 mg of potassium bitartrate in each gram (1.8%, 1%, and 0.4%, respectively) of off-white to tan color gel supplied in a pre-filled single-dose (5 grams) vaginal applicator

5 WARNINGS AND PRECAUTIONS

5.1 Cystitis and Pyelonephritis

Among 2804 subjects who received PHEXX in Studies 1 and 2, 0.36% (n=10) reported adverse reactions of cystitis, pyelonephritis, or other upper urinary tract infection (UTI). Of these, one case of pyelonephritis was considered serious and required hospitalization. Avoid use of PHEXX in females of reproductive potential with a history of recurrent urinary tract infection or urinary tract abnormalities.

6 ADVERSE REACTIONS

The following clinically significant adverse reactions are described elsewhere in the labeling:

- Cystitis and Pyelonephritis [see Warnings and Precautions (5.1)]

6.1 Clinical Trials Experience

Because clinical trials are conducted under widely varying conditions, adverse reaction rates observed in the clinical trials of a drug cannot be directly compared to rates in the clinical trials of another drug and may not reflect the rates observed in practice.

The safety of PHEXX (pre-filled applicator with 5-gram dose) has been evaluated in two clinical trials (Study 1 and Study 2) in 2804 subjects (over 19,000 cycles of exposure). The racial/ethnic distribution was 66% White, 27% Black or African American, 2% Asian, 1% American Indian or Alaska Native, 0.3% Native Hawaiian or Pacific Islander, and 5% other; 32% of the study population was Hispanic. Study 1 included a one-year extension phase where 342 U.S. subjects were exposed to PHEXX for 13 cycles.

Hypersensitivity Reaction

Of the 2804 PHEXX-treated subjects in Studies 1 and 2, one subject reported a suspected drug hypersensitivity. Avoid PHEXX use in females of reproductive potential with suspected hypersensitivity to the ingredients in PHEXX.

The most common adverse reactions (≥10%) in the U.S. population in Studies 1 and 2 (n=2480) were: vulvovaginal burning sensation (18.0%) and vulvovaginal pruritus (14.5%). The majority of these adverse reactions were mild and few led to discontinuation. Table 1 summarizes the most common adverse reactions (≥2%) reported by subjects using PHEXX in the U.S.

Table 1. Adverse Reactions that Occurred in ≥2% of Subjects Who Used PHEXX to Prevent Pregnancy (Studies 1 and 2 – U.S. population only)
Adverse Reaction | PHEXX (N=2480) (%)
Vulvovaginal Burning Sensation | 18.0
Vulvovaginal Pruritus | 14.5
Vulvovaginal Mycotic Infection [Includes preferred terms (PT) vulvovaginal mycotic infection and vulvovaginal candidiasis.] | 9.1
Urinary Tract Infection [Includes PTs urinary tract infection, streptococcal urinary tract infection, Escherichia urinary tract infection, and urinary tract infection bacterial.] [Does not include PTs cystitis, kidney infection, and pyelonephritis [see Warnings and Precautions (5.1)].] | 9.0
Vulvovaginal Discomfort | 9.0
Bacterial Vaginosis | 8.4
Vaginal Discharge | 5.5
Genital Discomfort | 4.1
Dysuria | 3.1
Vulvovaginal Pain | 2.1

Among subjects who used PHEXX in Studies 1 and 2, 1.6% discontinued from the clinical trials due to an adverse reaction. The most common adverse reactions leading to study discontinuation were vulvovaginal burning sensation (0.7%); and vulvovaginal pruritus and vulvovaginal discomfort (0.1% each).

Adverse Reactions in Male Partners

Among male partners of subjects who used PHEXX for contraception in Study 2, 9.8% (131 of 1330) reported symptoms of local discomfort (burning, itching, pain, and "other"). Of these local discomfort symptoms, 74.7% were mild, 21.4% were moderate, and 3.9% were severe. Two subjects discontinued participation in the study due to male partner symptoms.

8 USE IN SPECIFIC POPULATIONS

8.1 Pregnancy

Risk Summary

There is no use for PHEXX in pregnancy; therefore, discontinue PHEXX during pregnancy. There are no data with the use of PHEXX in pregnant women or animals. In the U.S. general population, the estimated background risk of major birth defects and miscarriage in clinically recognized pregnancies is 2 to 4 percent and 15 to 20 percent, respectively.

8.2 Lactation

Risk Summary

There are no data on the presence of lactic acid, citric acid, and potassium bitartrate or their metabolites in human milk, the effects on the breastfed infant, or the effects on milk production.

8.4 Pediatric Use

The safety and effectiveness of PHEXX have been established in females of reproductive potential. Efficacy is expected to be the same for post-menarchal females under the age of 17 as for users 17 years and older. The use of PHEXX before menarche is not indicated.

11 DESCRIPTION

PHEXX (lactic acid, citric acid, and potassium bitartrate) is a vaginal gel.

PHEXX is an off-white to tan in color gel of uniform consistency, containing three active ingredients: lactic acid, citric acid, and potassium bitartrate.

The structural formula for lactic acid is:

Lactic acid is designated chemically as 2-hydroxypropanoic acid with an empirical formula of C3H6O3 and a molecular weight of 90.08 g/mol.

The structural formula for citric acid is:

Citric acid is designated chemically as 2-hydroxypropane-1,2,3-tricarboxylic acid with an empirical formula of C6H8O7 and a molecular weight of 192.124 g/mol.

The structural formula for potassium bitartrate is:

Potassium bitartrate is designated chemically as potassium; (2R, 3R)-2,3,4-trihydroxy-4-oxobutanoate with an empirical formula of KC4H5O6 and a molecular weight of 188.177 g/mol.

Each 5 gram dose is provided in a pre-filled single-dose applicator containing lactic acid USP (1.8% w/w), citric acid USP (1% w/w), and potassium bitartrate USP (0.4% w/w). Inactive ingredients present in the gel are: glycerin, alginic acid, xanthan gum, sodium hydroxide, benzoic acid, and purified water.

12 CLINICAL PHARMACOLOGY

12.1 Mechanism of Action

In in vitro studies, PHEXX produced a normal vaginal pH range (pH 3.5 – 4.5) in the presence of semen. In clinical studies, post-coital testing demonstrated pH <5 in the majority of subjects, and sperm motility reduction.

12.2 Pharmacodynamics

Pharmacodynamic studies in humans have not been performed.

12.3 Pharmacokinetics

Pharmacokinetic studies in humans have not been performed. Systemic exposures of lactic acid, citric acid, and potassium bitartrate following vaginal administration of PHEXX are not expected to lead to safety concerns.

In vitro studies with commonly used vaginal preparations (miconazole, metronidazole, tioconazole, and a product for maintaining normal vaginal pH) showed no significant effect on the pH or buffering capacity of PHEXX.

13 NONCLINICAL TOXICOLOGY

13.1 Carcinogenesis, Mutagenesis, Impairment of Fertility

Carcinogenesis

Long-term carcinogenicity studies have not been performed with PHEXX.

Mutagenesis

Mutagenic studies have not been performed with PHEXX.

Impairment of Fertility

Reproductive studies have not been performed with PHEXX. Upon discontinuation of PHEXX, pregnancy may occur.

14 CLINICAL STUDIES

The efficacy of PHEXX for the prevention of pregnancy was evaluated in a multi-center, open-label, single-arm clinical trial in the United States (AMP002; NCT03243305). The study enrolled females of reproductive potential 18 to 35 years of age with regular menstrual cycles (21 to 35 days). The median age was 27.8 years. The racial distribution was 70.6% White, 23.7% Black or African American, 2.5% Asian, 0.4% American Indian or Alaska Native, 0.2% Native Hawaiian or Pacific Islander, and 2.7% other. Subjects agreed to engage in at least 3 acts of heterosexual, vaginal intercourse per cycle. Subjects self-administered a 5 gram dose of PHEXX intravaginally up to one hour before each episode of intercourse for up to 7 cycles.

The primary efficacy endpoint was the 7-cycle typical use cumulative pregnancy rate as derived by Kaplan-Meier life-table analysis. A total of 101 on-treatment pregnancies occurred in 1183 subjects contributing 4769 evaluable natural cycles. The 7-cycle cumulative pregnancy rate was 13.7% (95% CI: 10.0%, 17.5%), excluding cycles with back-up contraception, cycles <21 days or >35 days in length and cycles in which no intercourse was reported. The estimated Pearl Index, calculated based on data from the 7-cycle study, was 27.5 (95% CI: 22.4%, 33.5%).

16 HOW SUPPLIED/STORAGE AND HANDLING

PHEXX (lactic acid, citric acid, and potassium bitartrate) vaginal gel is an off-white to tan color gel of uniform consistency containing lactic acid (1.8%), citric acid (1%), and potassium bitartrate (0.4%), supplied as individually wrapped 5 gram pre-filled single-dose vaginal applicators in sealed foil pouches along with a plunger, and are available as follows:

- NDC 69751-101-12 | Box of 12 units

STORAGE AND HANDLING

Store in the original foil pack at room temperature 20°C to 25°C (68°F to 77°F); excursion permitted between 15°C to 30°C (59°F to 86°F) [see USP Controlled Room Temperature].

17 PATIENT COUNSELING INFORMATION

Advise the patient to read the Patient Information and FDA-approved patient labeling (Instructions for Use). Advise the patient:

- To intravaginally administer the contents of one pre-filled single-dose applicator of PHEXX before each episode of vaginal intercourse and to administer an additional dose if intercourse does not occur within one hour of administration [see Dosage and Administration (2.1)].
- To consult their healthcare provider for severe or prolonged genital irritation [see Adverse Reactions (6.1)].
- To discontinue PHEXX if they develop a local hypersensitivity reaction [see Adverse Reactions (6.1)].
- To contact their healthcare provider if experiencing urinary tract symptoms [see Warnings and Precautions (5.1)].
- That PHEXX does not protect against HIV infection and other sexually transmitted infections.

Manufactured for Evofem, Inc., a wholly owned subsidiary of Evofem Biosciences, Inc., San Diego, CA 92130

© 2025 Evofem, Inc.
U.S. Patents 6,706,276 and 10,568,855

All rights reserved.
PN-5067 R01

PATIENT INFORMATION

PHEXX® (FEX)
(lactic acid, citric acid, and potassium bitartrate) vaginal gel

For Vaginal Use Only

What is PHEXX?

- PHEXX is a prescription medicine used to prevent pregnancy in females who can become pregnant and choose to use an on-demand method of birth control.
- PHEXX is not effective at preventing pregnancy when used after vaginal sex.

How well does PHEXX work?

Your chance of getting pregnant depends on how well you follow the directions for using PHEXX. The better you follow the directions, the less chance you have of getting pregnant. It is very important that you follow the directions carefully each time you have vaginal sex.

PHEXX does not protect against HIV infection or other sexually transmitted infections (STIs).

Before using PHEXX, tell your healthcare provider about all of your medical conditions, including if you:

- are pregnant or think you are pregnant. PHEXX is not for use in pregnant women.
- are breastfeeding or plan to breastfeed. It is not known if PHEXX passes into your breast milk.

Tell your healthcare provider about all the medicines you take, including prescription and over-the-counter medicines, vitamins, and herbal supplements.

Know the medicines you take. Keep a list of them to show your healthcare provider and pharmacist when you get a new medicine.

How should I use PHEXX?

- See the Instructions for Use that come with PHEXX for detailed instructions on the right way to use PHEXX.
- Use PHEXX exactly as your healthcare provider tells you to use it.
- PHEXX must be used before vaginal sex.
- PHEXX comes as a pre-filled single-dose vaginal applicator.
- Insert 1 PHEXX pre-filled applicator into your vagina and use PHEXX within 1 hour before each time you have vaginal sex. If you do not have vaginal sex within 1 hour of using PHEXX, you must insert a new PHEXX pre-filled applicator.
- If you have vaginal sex more than 1 time within 1 hour, you must use a new PHEXX pre-filled applicator.
- PHEXX may be used at any time during the menstrual cycle.
- PHEXX may be used as soon as your healthcare provider tells you it is safe for you to have vaginal sex after childbirth, abortion, or miscarriage.
- PHEXX may be used with hormonal contraceptives; and latex, polyurethane, and polyisoprene condoms. PHEXX may be used with a vaginal diaphragm. Avoid using PHEXX with contraceptive vaginal rings.
- PHEXX may be used with other medicines used in the vagina to treat infections including miconazole, metronidazole, and tioconazole.

What are the possible side effects of PHEXX?

PHEXX may cause serious side effects, including:

- Bladder infection (cystitis) and acute kidney infection (pyelonephritis). Urinary tract infections are common but can also be serious. You should not use PHEXX if you have a history of urinary tract infections that keep coming back or other problems with your urinary tract. Call your healthcare provider if you have burning with urination or other signs and symptoms of a urinary tract infection such as: burning feeling when passing urine, urine that looks cloudy, pain in the pelvis, or back pain.
- Allergic reactions. Avoid using PHEXX if you are a female who can become pregnant and are allergic to lactic acid, citric acid, potassium bitartrate or any of the ingredients in PHEXX; or your sexual partners are allergic to any of the ingredients in PHEXX. Stop using PHEXX if you have a local vulvovaginal reaction.

The most common side effects of PHEXX include:

- vaginal burning
- vaginal itching
- vaginal yeast infection
- discomfort around the vaginal area
- bacterial vaginosis
- vaginal discharge
- discomfort in the genital area
- pain while passing urine

These are not all the possible side effects of PHEXX.

Call your healthcare provider for medical advice about side effects. You may report side effects to FDA at 1-800-FDA-1088.

How should I store PHEXX?

- Store PHEXX at room temperature between 68°F to 77°F (20°C to 25°C).
- Store PHEXX in the original foil pouch.

Keep PHEXX and all medicines out of the reach of children.

General information about the safe and effective use of PHEXX.

Medicines are sometimes used for purposes other than those listed in a Patient Information leaflet. Do not use PHEXX for a condition for which it was not prescribed. Do not give PHEXX to other people, even if they have the same symptoms that you have. It may harm them.

You can ask your healthcare provider or pharmacist for information about PHEXX that is written for health professionals.

What are the ingredients in PHEXX?

Active ingredients: lactic acid, citric acid, and potassium bitartrate

Inactive ingredients: glycerin, alginic acid, xanthan gum, sodium hydroxide, benzoic acid, and purified water

For more information, go to www.phexx.com or call 1-833-EVFMBIO.

Manufactured for Evofem, Inc., a wholly owned subsidiary of Evofem Biosciences, Inc.

Unless otherwise indicated, all trademarks used herein are the property of Evofem Biosciences, Inc.

This Patient Information has been approved by the U.S. Food and Drug Administration.

© 2025 Evofem, Inc.
All rights reserved.

Issued: April 2025
PN-5067 R01

INSTRUCTIONS FOR USE

PHEXX® (FEX)
(lactic acid, citric acid, and potassium bitartrate) vaginal gel

For Vaginal Use Only

These Instructions for Use contain information on how to use PHEXX vaginal gel.

Make sure that you read, understand, and follow the Instructions for Use before using PHEXX and each time you get a refill. There may be new information.

Contents:

- Each box contains 12 foil pouches.
- Each foil pouch contains a pre-filled applicator and plunger rod (see Figure A).
- Each pre-filled applicator contains 1 dose of PHEXX for 1-time use (single use).

Figure A

Important Information You Need to Know Before Using PHEXX

- Use 1 dose of PHEXX within 1 hour before you have vaginal sex.
- A new PHEXX pre-filled applicator must be used each time you have vaginal sex. If you have vaginal sex more than 1 time within 1 hour, a new PHEXX pre-filled applicator must be used.

Prepare to Use PHEXX

Keep the pre-filled applicator and plunger rod in the foil pouch until you are ready to use PHEXX.

Step 1: Wash Your Hands

- Wash your hands with soap and water before opening the foil pouch.

Step 2: Remove the Pre-filled Applicator and Plunger Rod from the Foil Pouch

- Remove the pre-filled applicator and plunger rod from the foil pouch (see Figure B).

Figure B

Important: Do not remove the pink cap until instructed in Step 4.

Insert PHEXX Gel

Step 3: Insert the Plunger Rod

- Gently and slowly insert the plunger rod into the pre-filled applicator. Push until you feel the tip of the plunger rod connect to the inside of the pre-filled applicator (see Figure C).

Figure C

- Do not push hard or continue to push after the tip of the plunger rod connects to the inside of the pre-filled applicator. This could cause the gel to go into the pink cap.
- Use a new pre-filled applicator if the gel goes into the pink cap.

Step 4: Remove the Pink Cap

- After the plunger rod is connected to the pre-filled applicator, remove the pink cap from the pre-filled applicator (see Figure D).
- The extra space between the gel and the end of the pre-filled applicator is normal.
- The pre-filled applicator is now ready for use.

Figure D

Step 5: Insert the PHEXX Pre-filled Applicator into the Vagina

- Hold the pre-filled applicator at the grooved area closest to the plunger rod (see Figure E).

Figure E

- Gently insert the pre-filled applicator into the vagina as far as it will comfortably go while you continue to hold it by the grooved area firmly. This can be done sitting with your knees apart, lying on your back with your knees bent (see Figure F), or while standing with your feet apart or knees bent.

Figure F

Step 6: Insert PHEXX Gel

- While the pre-filled applicator is inserted in your vagina, use your index finger to push the plunger rod down until it stops. This is to make sure you receive the entire dose of PHEXX (see Figure G).
- It is normal for a small amount of gel to be left in the applicator. You will still get the right dose.

Figure G

Step 7: Remove the Used PHEXX Pre-filled Applicator

- Gently remove the plunger rod and pre-filled applicator from the vagina (see Figure H) and throw away (dispose of) the used pre-filled applicator.
- PHEXX should be used within 1 hour before each time you have vaginal sex. Use a new pre-filled applicator if you do not have vaginal sex within 1 hour of inserting PHEXX gel and you still plan to have vaginal sex.

Figure H

Disposing of PHEXX

Step 8: Throw Away (Dispose of) the Used PHEXX Pre-filled Applicator

- Used PHEXX pre-filled applicators and caps should be disposed of in the trash. The cap may be a potential choking hazard.

Storing PHEXX

- Store PHEXX at room temperature between 68°F to 77°F (20°C to 25°C).
- Store PHEXX in the original foil pouch.

Keep PHEXX and all medicines out of the reach of children.

These Instructions for Use have been approved by the U.S. Food and Drug Administration.

For more information, including full prescribing information and information on patient safety, go to www.phexx.com or call 1-833-EVFMBIO.

Manufactured for Evofem, Inc., a wholly owned subsidiary of Evofem Biosciences, Inc.

© 2025 Evofem, Inc. All rights reserved.

Issued: April 2025

PRINCIPAL DISPLAY PANEL - 12 Applicator Box

phexx®

(lactic acid, citric acid, and
potassium bitartrate) Vaginal Gel
1.8%, 1%, 0.4%

NDC 69751-101-12
PN-5065 R01